DRUG LABEL: Intellishade TruPhysical Clear SPF 50
NDC: 64651-1226 | Form: CREAM
Manufacturer: Revision, LLC
Category: otc | Type: HUMAN OTC DRUG LABEL
Date: 20260113

ACTIVE INGREDIENTS: TITANIUM DIOXIDE 2.5 g/100 g; ZINC OXIDE 15.2 g/100 g
INACTIVE INGREDIENTS: MAGNESIUM CHLORIDE; XANTHAN GUM; WATER; MEDIUM-CHAIN TRIGLYCERIDES; THERMUS THERMOPHILUS; DIISOPROPYL ADIPATE; POLYGLYCERYL-2 DIPOLYHYDROXYSTEARATE; C12-20 ALKYL BENZOATE; CYCLOMETHICONE 5; DIMETHICONE; POLYGLYCERYL-3 DIISOSTEARATE; GLYCERIN; HYDROGENATED STARCH HYDROLYSATE; BUTYLENE GLYCOL; POLYHYDROXYSTEARIC ACID (2300 MW); GLYCERYL ISOSTEARATE; SILICON DIOXIDE; ALOE VERA LEAF; BETULA PUBESCENS BARK; GREEN TEA LEAF; 2-ETHYLHEXYL ACRYLATE, METHACRYLATE, METHYL METHACRYLATE, OR BUTYL METHACRYLATE/HYDROXYPROPYL DIMETHICONE COPOLYMER (30000-300000 MW); SQUALANE; .ALPHA.-TOCOPHEROL ACETATE, DL-; TETRAHEXYLDECYL ASCORBATE; .ALPHA.-TOCOPHEROL; PALMITOYL TRIPEPTIDE-5; DIMETHICONE/VINYL DIMETHICONE CROSSPOLYMER (SOFT PARTICLE); LECITHIN, SOYBEAN; PALMITOYLLYSYLVALYLDIAMINOBUTYROYLTHREONINE; LEUCONOSTOC/RADISH ROOT FERMENT FILTRATE; TETRADECYL AMINOBUTYROYLVALYLAMINOBUTYRIC UREA TRIFLUOROACETATE; YEAST, UNSPECIFIED; BORON NITRIDE; EPIGALLOCATECHIN GALLATE; UBIDECARENONE; SIMMONDSIA CHINENSIS SEED; MELANIN SYNTHETIC (TYROSINE, PEROXIDE); PHENOXYETHANOL; GLYCERYL BEHENATE/EICOSADIOATE; SORBIC ACID; MAGNESIUM SULFATE HEPTAHYDRATE; CHLORPHENESIN; STEAROYL GLUTAMIC ACID; BENZOIC ACID; FERRIC OXIDE YELLOW

Intellishade TruPhysical Clear SPF 50

1.7oz Revision Intellishade® Original

ITPC_carton_retail_ITCC3_V1_OL (1)

ITPC_pro_tube_ITCP3_V2_OL (1)

Intellishade®
Original

anti-aging
tinted moisturizer
with sunscreen

Broad-Spectrum
SPF 45

NET WT 1.7 OZ | 48 g

Active ingredient Purpose
Titanium Dioxide 2.5%........ Sunscreen
Zinc Oxide 15.2% ............... Sunscreen

Uses
• helps prevent sunburn
• if used as directed with other sun protection measures (see Directions), decreases the risk of skin cancer
and early skin aging caused by the sun

Warnings
For external use only

Do not useon damaged or broken skin

WHEN USING

When using this productkeep out of eyes. Rinse with water to remove.

Stop use and ask a doctorif rash occurs

Keep out of reach of children.If swallowed, get medical help or contact a Poison Control Center right away.

Directions
• apply liberally 15 minutes before sun exposure
• reapply at least every 2 hours
• use a water resistant sunscreen if swimming or sweating
• Sun Protection Measures.
Spending time in the sun increases your risk of skin cancer and early skin aging. To decrease
this risk, regularly use a sunscreen with a Broad-Spectrum SPF value of 15 or higher and
other sun protection measures including:
• limit time in the sun, especially from 10 a.m. – 2 p.m.
• wear long-sleeved shirts, pants, hats, and sunglasses
• children under 6 months: Ask a doctor

Inactive ingredients

Water (Aqua), Caprylic/Capric Triglyceride, Thermus Thermophillus Ferment, Diisopropyl Adipate, Polyglyceryl-2 Dipolyhydroxystearate, C12-15 Alkyl Benzoate, Bacillus Lysate, Cyclopentasiloxane, Dimethicone, Polyglyceryl-3 Diisostearate, Glycerin, Hydrogenated Starch Hydrolysate, Butylene Glycol, Polyhydroxystearic Acid, Glyceryl Isostearate, Silica, Aloe Barbadensis Leaf Juice, Betula Alba Bark Extract, Camellia Sinensis Leaf Extract, Plankton Extract, Acrylates/Dimethicone Copolymer, Squalane, Tocopheryl Acetate, Tetrahexyldecyl Ascorbate, Tocopherol, Palmitoyl Tripeptide-5, Dimethicone/Vinyl Dimethicone Crosspolymer, Lecithin, Palmitoyl Dipeptide-5 Diaminobutyroyl Hydroxythreonine, Leuconostoc/Radish Root Ferment Filtrate, Tetradecyl Aminobutyroylvalylaminobutyric Urea Acetate, Yeast Extract (Faex), Boron Nitride, Epigallocatechin Gallate, Ubiquinone, Simmondsia Chinensis (Jojoba) Meal Extract, Melanin, Phenoxyethanol, Glyceryl Behenate/Eicosadioate, Chlorphenesin, Stearoyl Glutamic Acid, Xanthan Gum, Magnesium Chloride, Benzoic Acid, Sorbic Acid, Magnesium Sulfate, Iron Oxides (CI 77492)

Other information
• protect this product from excessive heat and direct sun

Dist. by Revision, LP
Irving, TX 75063 Made in U.S.A.

8oz Revision Intellishade® Original

ITPC_retail_tube_ITCR4_V1_OL (1)

Intellishade®
Original

anti-aging
tinted moisturizer
with sunscreen

Broad-Spectrum
SPF 45

NET WT 8 OZ | 227 g

Active ingredient Purpose
Titanium Dioxide 2.5%........ Sunscreen
Zinc Oxide 15.2% ............... Sunscreen

Uses
• helps prevent sunburn
• if used as directed with other sun protection measures (see Directions), decreases the risk of skin cancer
and early skin aging caused by the sun

Warnings
For external use only

Do not useon damaged or broken skin

WHEN USING

When using this productkeep out of eyes. Rinse with water to remove.

Stop use and ask a doctorif rash occurs

Keep out of reach of children.If swallowed, get medical help or contact a Poison Control Center right away.

Directions
• apply liberally 15 minutes before sun exposure
• reapply at least every 2 hours
• use a water resistant sunscreen if swimming or sweating
• Sun Protection Measures.
Spending time in the sun increases your risk of skin cancer and early skin aging. To decrease
this risk, regularly use a sunscreen with a Broad-Spectrum SPF value of 15 or higher and
other sun protection measures including:
• limit time in the sun, especially from 10 a.m. – 2 p.m.
• wear long-sleeved shirts, pants, hats, and sunglasses
• children under 6 months: Ask a doctor

Inactive ingredients

Water (Aqua), Caprylic/Capric Triglyceride, Thermus Thermophillus Ferment, Diisopropyl Adipate, Polyglyceryl-2 Dipolyhydroxystearate, C12-15 Alkyl Benzoate, Bacillus Lysate, Cyclopentasiloxane, Dimethicone, Polyglyceryl-3 Diisostearate, Glycerin, Hydrogenated Starch Hydrolysate, Butylene Glycol, Polyhydroxystearic Acid, Glyceryl Isostearate, Silica, Aloe Barbadensis Leaf Juice, Betula Alba Bark Extract, Camellia Sinensis Leaf Extract, Plankton Extract, Acrylates/Dimethicone Copolymer, Squalane, Tocopheryl Acetate, Tetrahexyldecyl Ascorbate, Tocopherol, Palmitoyl Tripeptide-5, Dimethicone/Vinyl Dimethicone Crosspolymer, Lecithin, Palmitoyl Dipeptide-5 Diaminobutyroyl Hydroxythreonine, Leuconostoc/Radish Root Ferment Filtrate, Tetradecyl Aminobutyroylvalylaminobutyric Urea Acetate, Yeast Extract (Faex), Boron Nitride, Epigallocatechin Gallate, Ubiquinone, Simmondsia Chinensis (Jojoba) Meal Extract, Melanin, Phenoxyethanol, Glyceryl Behenate/Eicosadioate, Chlorphenesin, Stearoyl Glutamic Acid, Xanthan Gum, Magnesium Chloride, Benzoic Acid, Sorbic Acid, Magnesium Sulfate, Iron Oxides (CI 77492)

Other information
• protect this product from excessive heat and direct sun

Dist. by Revision, LP
Irving, TX 75063 Made in U.S.A.

DOSAGE AND ADMINISTRATION

apply liberally 15 minutes before sun exposure
reapply at least every two hours
use a water resistant sunscreen if swimming or sweating

PURPOSE

Anti-aging untinted daily moisturizer with 100% mineral sunscreen

Broad Spectrum

SPF 50